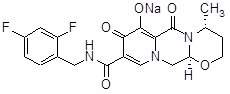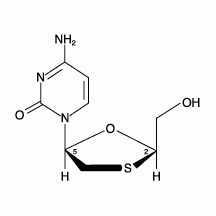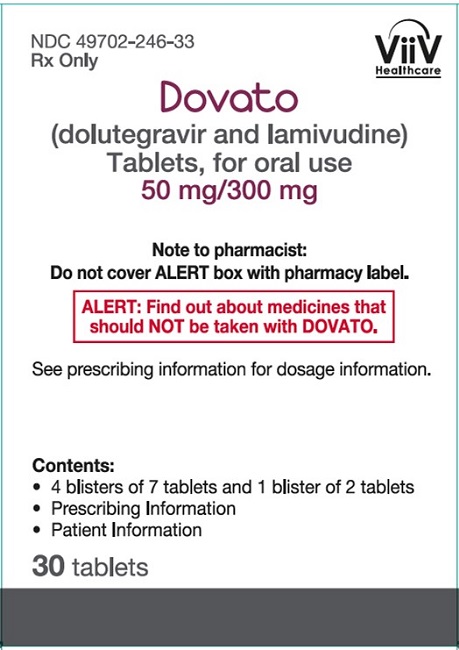 DRUG LABEL: Dovato
NDC: 49702-246 | Form: TABLET, FILM COATED
Manufacturer: ViiV Healthcare Company
Category: prescription | Type: HUMAN PRESCRIPTION DRUG LABEL
Date: 20251029

ACTIVE INGREDIENTS: DOLUTEGRAVIR SODIUM 50 mg/1 1; LAMIVUDINE 300 mg/1 1
INACTIVE INGREDIENTS: MAGNESIUM STEARATE; MANNITOL; MICROCRYSTALLINE CELLULOSE; POVIDONE K30; SODIUM STARCH GLYCOLATE TYPE A CORN; SODIUM STEARYL FUMARATE; HYPROMELLOSE, UNSPECIFIED; POLYETHYLENE GLYCOL, UNSPECIFIED; TITANIUM DIOXIDE

HIGHLIGHTS OF PRESCRIBING INFORMATION

These highlights do not include all the information needed to use DOVATO safely and effectively. See full prescribing information for DOVATO.
DOVATO (dolutegravir and lamivudine) tablets, for oral use
Initial U.S. Approval: 2019

WARNING: PATIENTS CO-INFECTED WITH HEPATITIS B VIRUS (HBV) AND HUMAN IMMUNODEFICIENCY VIRUS (HIV-1): EMERGENCE OF LAMIVUDINE-RESISTANT HBV AND EXACERBATIONS OF HBV

See full prescribing information for complete boxed warning.

- All patients with HIV-1 should be tested for the presence of HBV prior to or when initiating DOVATO. Emergence of lamivudine-resistant HBV variants associated with lamivudine-containing antiretroviral regimens has been reported. If DOVATO is used in patients co-infected with HIV-1 and HBV, additional treatment should be considered for appropriate treatment of chronic HBV; otherwise, consider an alternative regimen.
- Severe acute exacerbations of HBV have been reported in patients who are co-infected with HIV-1 and HBV and have discontinued lamivudine, a component of DOVATO. Closely monitor hepatic function in these patients and, if appropriate, initiate anti-HBV treatment. (5.1)

1 INDICATIONS AND USAGE

DOVATO, a two-drug combination of dolutegravir (integrase strand transfer inhibitor [INSTI]) and lamivudine (nucleoside analogue reverse transcriptase inhibitor [NRTI]) is indicated as a complete regimen for the treatment of HIV-1 infection in adults and adolescents 12 years of age and older and weighing at least 25 kg with no antiretroviral treatment history or to replace the current antiretroviral regimen in those who are virologically suppressed (HIV-1 RNA less than 50 copies/mL) on a stable antiretroviral regimen with no history of treatment failure and no known substitutions associated with resistance to the individual components of DOVATO. (1)

2 DOSAGE AND ADMINISTRATION

- Prior to or when initiating DOVATO, test patients for hepatitis B virus (HBV) infection. (2.1)
- One tablet taken orally once daily with or without food. (2.2)
- The dolutegravir dose (50 mg) in DOVATO is insufficient when coadministered with carbamazepine or rifampin. If DOVATO is coadministered with carbamazepine or rifampin, take one tablet of DOVATO once daily, followed by an additional dolutegravir 50-mg tablet, approximately 12 hours from the dose of DOVATO. (2.3)

3 DOSAGE FORMS AND STRENGTHS

Tablets: 50 mg of dolutegravir and 300 mg of lamivudine. (3)

4 CONTRAINDICATIONS

- Prior hypersensitivity reaction to dolutegravir or lamivudine. (4)
- Coadministration with dofetilide. (4)

5 WARNINGS AND PRECAUTIONS

- Hypersensitivity reactions characterized by rash, constitutional findings, and sometimes organ dysfunction, including liver injury, have been reported with dolutegravir. Discontinue DOVATO immediately if signs or symptoms of hypersensitivity reactions develop, as a delay in stopping treatment may result in a life-threatening reaction. (5.2)
- Hepatotoxicity has been reported in patients receiving a dolutegravir-containing regimen. Patients with underlying hepatitis B or C may be at increased risk for worsening or development of transaminase elevations with DOVATO. Monitoring for hepatotoxicity is recommended. (5.3)
- Lactic acidosis and severe hepatomegaly with steatosis, including fatal cases, have been reported with the use of nucleoside analogues. (5.4)
- Immune reconstitution syndrome has been reported in patients treated with combination antiretroviral therapy. (5.6)

6 ADVERSE REACTIONS

The most common adverse reactions (all grades) observed in ≥2% (in those receiving DOVATO) were headache, nausea, diarrhea, insomnia, fatigue, and anxiety. (6.1)

To report SUSPECTED ADVERSE REACTIONS, contact ViiV Healthcare at 1-877-844-8872 or FDA at 1-800-FDA-1088 or www.fda.gov/medwatch.

7 DRUG INTERACTIONS

- DOVATO is a complete regimen for the treatment of HIV-1 infection; therefore, coadministration with other antiretroviral drugs for the treatment of HIV-1 infection is not recommended. (7.1)
- Refer to the full prescribing information for important drug interactions with DOVATO. (4, 5.5, 7)

8 USE IN SPECIFIC POPULATIONS

- Renal impairment: DOVATO is not recommended in patients with creatinine clearance less than 30 mL/min. (8.6)
- Hepatic impairment: DOVATO is not recommended in patients with severe hepatic impairment (Child-Pugh Score C). (8.7)

FULL PRESCRIBING INFORMATION

WARNING: PATIENTS CO-INFECTED WITH HEPATITIS B VIRUS (HBV) AND HUMAN IMMUNODEFICIENCY VIRUS (HIV-1): EMERGENCE OF LAMIVUDINE-RESISTANT HBV AND EXACERBATIONS OF HBV

All patients with HIV-1 should be tested for the presence of HBV prior to or when initiating DOVATO. Emergence of lamivudine-resistant HBV variants associated with lamivudine-containing antiretroviral regimens has been reported. If DOVATO is used in patients co-infected with HIV-1 and HBV, additional treatment should be considered for appropriate treatment of chronic HBV; otherwise, consider an alternative regimen.

Severe acute exacerbations of HBV have been reported in patients who are co-infected with HIV-1 and HBV and have discontinued lamivudine, a component of DOVATO. Closely monitor hepatic function in these patients and, if appropriate, initiate anti-HBV treatment [see Warnings and Precautions (5.1)].

1 INDICATIONS AND USAGE

DOVATO is indicated as a complete regimen for the treatment of HIV-1 infection in adults and adolescents 12 years of age and older and weighing at least 25 kg with no antiretroviral treatment history or to replace the current antiretroviral regimen in those who are virologically suppressed (HIV-1 RNA less than 50 copies/mL) on a stable antiretroviral regimen with no history of treatment failure and no known substitutions associated with resistance to the individual components of DOVATO.

2 DOSAGE AND ADMINISTRATION

2.1 Testing Prior to or When Initiating Treatment with DOVATO

Prior to or when initiating DOVATO, test patients for HBV infection [see Warnings and Precautions (5.1)].

2.2 Recommended Dosage

DOVATO is a fixed-dose combination product containing 50 mg of dolutegravir and 300 mg of lamivudine. The recommended dosage regimen of DOVATO in adults and adolescents 12 years of age and older and weighing at least 25 kg is one tablet taken orally once daily with or without food [see Clinical Pharmacology (12.3)].

2.3 Recommended Dosage with Certain Coadministered Drugs

The dolutegravir dose (50 mg) in DOVATO is insufficient when coadministered with drugs listed in Table 1 that may decrease dolutegravir concentrations; the following dolutegravir dosage regimen is recommended.

Table 1. Dosing Recommendations for DOVATO with Coadministered Drugs
Coadministered Drug | Dosing Recommendation
Carbamazepine, rifampin | An additional dolutegravir 50-mg tablet, separated by 12 hours from DOVATO, should be taken.

2.4 Not Recommended in Patients with Renal Impairment

Because DOVATO is a fixed-dose tablet and cannot be dose adjusted, DOVATO is not recommended in patients with creatinine clearance less than 30 mL/min [see Use in Specific Populations (8.6)].

2.5 Not Recommended in Patients with Severe Hepatic Impairment

DOVATO is not recommended in patients with severe hepatic impairment (Child-Pugh Score C) [see Use in Specific Populations (8.7)].

3 DOSAGE FORMS AND STRENGTHS

DOVATO tablets are oval, biconvex, white, film-coated tablets, debossed with “SV 137” on one face. Each tablet contains 50 mg of dolutegravir and 300 mg of lamivudine.

4 CONTRAINDICATIONS

DOVATO is contraindicated in patients:

- with prior hypersensitivity reaction to dolutegravir or lamivudine [see Warnings and Precautions (5.2)].
- receiving dofetilide due to the potential for increased dofetilide plasma concentrations and the risk for serious and/or life-threatening events [see Drug Interactions (7.2)].

5 WARNINGS AND PRECAUTIONS

5.1 Patients Co-infected with HIV-1 and HBV: Emergence of Lamivudine-Resistant HBV and the Risk of Posttreatment Exacerbations of HBV

All patients with HIV-1 should be tested for the presence of HBV prior to or when initiating DOVATO.

Emergence of Lamivudine-Resistant HBV

Safety and efficacy of lamivudine have not been established for treatment of chronic HBV in subjects dually infected with HIV-1 and HBV. Emergence of HBV variants associated with resistance to lamivudine has been reported in HIV‑1–infected subjects who have received lamivudine‑containing antiretroviral regimens in the presence of concurrent infection with HBV. If a decision is made to administer DOVATO to patients co-infected with HIV-1 and HBV, additional treatment should be considered for appropriate treatment of chronic HBV; otherwise, consider an alternative regimen.

Severe Acute Exacerbations of HBV in Patients Co-infected with HIV-1 and HBV

Severe acute exacerbations of HBV have been reported in patients who are co-infected with HIV-1 and HBV and have discontinued products containing lamivudine, and may occur with discontinuation of DOVATO. Patients who are co-infected with HIV-1 and HBV who discontinue DOVATO should be closely monitored with both clinical and laboratory follow-up for at least several months after stopping treatment with DOVATO. If appropriate, initiation of anti-HBV therapy may be warranted, especially in patients with advanced liver disease or cirrhosis, since posttreatment exacerbation of hepatitis may lead to hepatic decompensation and liver failure.

5.2 Hypersensitivity Reactions

Hypersensitivity reactions have been reported with the use of dolutegravir, a component of DOVATO, and were characterized by rash, constitutional findings, and sometimes organ dysfunction, including liver injury. These events were reported in <1% of subjects receiving dolutegravir in Phase 3 clinical trials.

Discontinue DOVATO immediately if signs or symptoms of hypersensitivity reactions develop (including, but not limited to, severe rash or rash accompanied by fever, general malaise, fatigue, muscle or joint aches, blisters or peeling of the skin, oral blisters or lesions, conjunctivitis, facial edema, hepatitis, eosinophilia, angioedema, difficulty breathing). Clinical status, including liver aminotransferases, should be monitored and appropriate therapy initiated. Delay in stopping treatment with DOVATO or other suspect agents after the onset of hypersensitivity may result in a life-threatening reaction [see Contraindications (4)].

5.3 Hepatotoxicity

Hepatic adverse events have been reported in patients receiving a dolutegravir-containing regimen [see Adverse Reactions (6.1)]. Patients with underlying hepatitis B or C may be at increased risk for worsening or development of transaminase elevations with use of DOVATO [see Adverse Reactions (6.1)]. In some cases, the elevations in transaminases were consistent with immune reconstitution syndrome or HBV reactivation particularly in the setting where anti-hepatitis therapy was withdrawn. Cases of hepatic toxicity, including elevated serum liver biochemistries, hepatitis, and acute liver failure, have also been reported in patients receiving a dolutegravir-containing regimen who had no pre-existing hepatic disease or other identifiable risk factors. Drug-induced liver injury leading to liver transplant has been reported with TRIUMEQ (abacavir, dolutegravir, and lamivudine). Monitoring for hepatotoxicity is recommended.

5.4 Lactic Acidosis and Severe Hepatomegaly with Steatosis

Lactic acidosis and severe hepatomegaly with steatosis, including fatal cases, have been reported with the use of nucleoside analogues, including lamivudine (a component of DOVATO). A majority of these cases have been in women. Female sex and obesity may be risk factors for the development of lactic acidosis and severe hepatomegaly with steatosis in patients treated with antiretroviral nucleoside analogues. Monitor closely when administering DOVATO to any patient with known risk factors for liver disease. Treatment with DOVATO should be suspended in any patient who develops clinical or laboratory findings suggestive of lactic acidosis or pronounced hepatotoxicity, which may include hepatomegaly and steatosis even in the absence of marked transaminase elevations.

5.5 Risk of Adverse Reactions or Loss of Virologic Response Due to Drug Interactions

The coadministration of DOVATO and other drugs may result in known or potentially significant drug interactions, some of which may lead to [see Contraindications (4), Drug Interactions (7.4)]:

- Loss of therapeutic effect of DOVATO and possible development of resistance.
- Possible clinically significant adverse reactions from greater exposures of coadministered drugs.

See Table 5 for steps to prevent or manage these possible and known significant drug interactions, including dosing recommendations. Consider the potential for drug interactions prior to and during therapy with DOVATO, review coadministered drugs during therapy with DOVATO, and monitor for the adverse reactions associated with the coadministered drugs.

5.6 Immune Reconstitution Syndrome

Immune reconstitution syndrome has been reported in patients treated with combination antiretroviral therapy, including DOVATO. During the initial phase of combination antiretroviral treatment, patients whose immune systems respond may develop an inflammatory response to indolent or residual opportunistic infections (such as Mycobacterium avium infection, cytomegalovirus, Pneumocystis jirovecii pneumonia [PCP], or tuberculosis), which may necessitate further evaluation and treatment.

Autoimmune disorders (such as Graves’ disease, polymyositis, and Guillain-Barré syndrome) have also been reported to occur in the setting of immune reconstitution; however, the time to onset is more variable and can occur many months after initiation of treatment.

6 ADVERSE REACTIONS

The following adverse reactions are discussed in other sections of the labeling:

- Patients co-infected with HIV-1 and HBV [see Warnings and Precautions (5.1)]
- Hypersensitivity reactions [see Warnings and Precautions (5.2)]
- Hepatotoxicity [see Warnings and Precautions (5.3)]
- Lactic acidosis and severe hepatomegaly with steatosis [see Warnings and Precautions (5.4)]
- Immune reconstitution syndrome [see Warnings and Precautions (5.6)]

6.1 Clinical Trials Experience

Because clinical trials are conducted under widely varying conditions, adverse reaction rates observed in the clinical trials of a drug cannot be directly compared with rates in the clinical trials of another drug and may not reflect the rates observed in clinical practice.

Clinical Trials in Adults with No Antiretroviral Treatment History

The safety assessment of DOVATO in HIV-1–infected adults with no antiretroviral treatment history and with a plasma viral load ≤500,000 HIV-1 RNA copies/mL at the screening visit, is based on the pooled Week 144 analyses of data from 2 identical, multicenter, double-blind, controlled trials, GEMINI-1 and GEMINI-2. A total of 1,433 HIV-1–infected adults with no antiretroviral treatment history received either dolutegravir (TIVICAY) 50 mg plus lamivudine (EPIVIR) 300 mg, as a complete regimen once daily, or TIVICAY 50 mg plus fixed-dose combination tenofovir disoproxil fumarate (TDF)/emtricitabine (FTC) (TRUVADA), administered once daily.

The rates of adverse events leading to discontinuation in the pooled analysis were 4% of subjects who received TIVICAY plus EPIVIR and 5% in subjects who received TIVICAY plus TRUVADA. The most common adverse events leading to discontinuation were psychiatric disorders: 2% of subjects who received TIVICAY plus EPIVIR and 1% in subjects who received TIVICAY plus TRUVADA.

Adverse reactions (all grades) observed in at least 2% of subjects in either treatment arm of the Week 144 pooled analysis from GEMINI-1 and GEMINI-2 trials are provided in Table 2.

The adverse reactions observed for TIVICAY plus EPIVIR in the Week 144 analysis of the pooled data from GEMINI-1 and GEMINI-2 were generally consistent with the adverse reaction profiles and severities for the individual components when administered with other antiretroviral agents.

Table 2. Adverse Reactions (All Grades) Reported in ≥2% of Subjects in Any Treatment Group in Adults with No Antiretroviral Treatment History in GEMINI-1 and GEMINI-2 (Week 144 Pooled Analysis)
Adverse Reaction | TIVICAY plus EPIVIR; (n = 716) | TIVICAY plus TRUVADA; (n = 717)
Headache | 3% | 4%
Nausea | 2% | 6%
Diarrhea | 2% | 3%
Insomnia | 2% | 3%
Fatiguea | 2% | 2%
Anxiety | 2% | 1%
Dizziness | 1% | 2%
a Fatigue: includes fatigue, asthenia, and malaise.

Adverse reactions of at least Grade 2 occurring in ≥1% of subjects treated with TIVICAY plus EPIVIR were headache, anxiety, suicidal ideation, and insomnia (all at 1%).

Less Common Adverse Reactions: The following adverse reactions (all grades) occurred in <2% of subjects receiving dolutegravir plus lamivudine or are from studies described in the prescribing information of the individual components, TIVICAY (dolutegravir) and EPIVIR (lamivudine). Some events have been included because of their seriousness and assessment of potential causal relationship.

Blood and Lymphatic Systems Disorders: Anemia, neutropenia, thrombocytopenia.

Gastrointestinal Disorders: Abdominal discomfort, abdominal pain, flatulence, upper abdominal pain, vomiting.

General: Fever.

Hepatobiliary Disorders: Hepatitis.

Immune System Disorders: Hypersensitivity, immune reconstitution syndrome.

Musculoskeletal Disorders: Myositis.

Nervous System Disorders: Somnolence.

Psychiatric Disorders: Abnormal dreams, depression. Suicidal ideation, attempt, behavior, or completion; these events were observed primarily in subjects with a pre-existing history of depression or other psychiatric illness.

Renal and Urinary Disorders: Renal impairment.

Skin and Subcutaneous Tissue Disorders: Pruritus, rash.

Clinical Trials in Virologically Suppressed Adults

The safety of DOVATO in virologically suppressed adults was based on Week 144 data from 740 subjects in a randomized, parallel-group, open-label, multicenter, non-inferiority controlled trial (TANGO). Subjects who were on a stable suppressive tenofovir alafenamide-based regimen (TBR) were randomized to receive DOVATO once daily or continue with their TBR for up to 148 weeks; at Week 148, the subjects randomized to continue with their TBR were switched to DOVATO once daily. All subjects are followed up to Week 200. Overall, the safety profile of DOVATO in virologically suppressed adult subjects in the TANGO trial was similar to that of TIVICAY plus EPIVIR in subjects with no antiretroviral treatment history in the GEMINI trials [see Clinical Studies (14.3)]. Adverse reactions observed in at least 2% of subjects in the TANGO trial who were treated with DOVATO were weight increased (3%) and insomnia (2%).

Laboratory Abnormalities

Selected laboratory abnormalities with a worsening grade from baseline and representing the worst-grade toxicity are presented in Table 3. The mean change from baseline observed for selected lipid values is presented in Table 4.

Table 3. Selected Laboratory Abnormalities (Grades 2 to 4; Week 144 Pooled Analyses) in GEMINI-1 and GEMINI-2 Trials
Laboratory Parameter; Abnormality | TIVICAY plus EPIVIR; (n = 716) | TIVICAY plus TRUVADA; (n = 717)
Alanine aminotransferase (ALT)
Grade 2 (2.5 to <5.0 x ULN) | 4% | 4%
Grade 3 to 4 (≥5.0 x ULN) | 4% | 3%
Aspartate aminotransferase (AST)
Grade 2 (2.5 to <5.0 x ULN) | 5% | 5%
Grade 3 to 4 (≥5.0 x ULN) | 3% | 4%
Total bilirubin
Grade 2 (1.6 to <2.6 x ULN) | 3% | 4%
Grade 3 to 4 (≥2.6 x ULN) | 1% | 1%
Creatine kinase
Grade 2 (6.0 to <10 x ULN) | 5% | 5%
Grade 3 to 4 (≥10.0 x ULN) | 8% | 9%
Hyperglycemia (glucose)
Grade 2 (126 to 250 mg/dL) | 11% | 8%
Grade 3 to 4 (>250 mg/dL) | 1% | 1%
Hypophosphatemia (phosphate)
Grade 2 (1.4 to <2.0 mg/dL) | 11% | 12%
Grade 3 to 4 (<1.4 mg/dL) | 1% | 2%
Lipase
Grade 2 (1.5 to <3.0 x ULN) | 7% | 8%
Grade 3 to 4 (≥3.0 x ULN) | 3% | 5%
ULN = Upper limit of normal.

Table 4. Mean Change from Baseline in Fasted Lipid Values (Week 144 Pooled Analysesa) in GEMINI 1 and GEMINI 2 Trials
Laboratory Parameter; Preferred Term | TIVICAY plus EPIVIR; (n = 716) | TIVICAY plus TRUVADA; (n = 717)
Cholesterol (mg/dL) | 15 | -2
HDL cholesterol (mg/dL) | 7 | 4
LDL cholesterol (mg/dL) | 7 | -4
Triglycerides (mg/dL) | 10 | -9
Total cholesterol/HDL cholesterol ratio | -0.2 | -0.4
HDL = High density lipoprotein; LDL = Low density lipoprotein.
a Subjects on lipid-lowering agents at baseline are excluded (TIVICAY plus EPIVIR, n = 30; TIVICAY plus TRUVADA, n = 23). The last available fasted, on-treatment lipid value prior to initiation of a lipid-lowering agent was carried forward in place of observed values after initiation of a lipid-lowering agent. A total of 51 and 28 subjects receiving TIVICAY plus EPIVIR and TIVICAY plus TRUVADA, respectively, initiated lipid-lowering agents post-baseline.

Changes in Serum Creatinine: Dolutegravir has been shown to increase serum creatinine due to inhibition of tubular secretion of creatinine without affecting renal glomerular function [see Clinical Pharmacology (12.2)]. Increases in serum creatinine occurred within the first 4 weeks of treatment in both arms and remained stable through 144 weeks. A mean change from baseline of 0.144 mg/dL and 0.176 mg/dL was observed after 144 weeks of treatment with TIVICAY plus EPIVIR and TIVICAY plus TRUVADA, respectively. These changes are not considered to be clinically relevant.

Clinical Trial Experience in Adolescents

The safety of DOVATO was evaluated in HIV‑1–infected treatment-naïve subjects between 12 to less than 18 years of age and weighing at least 25 kg (N = 32) through Week 48, in an open label clinical trial, DANCE (Trial 205861). Overall, the observed safety profile in adolescent subjects was similar to those seen in adults [see Use in Specific Populations (8.4), and Clinical Studies (14.4)].

6.2 Postmarketing Experience

The following adverse reactions have been identified during postmarketing experience in patients receiving a dolutegravir- or lamivudine-containing regimen. Because postmarketing reactions are reported voluntarily from a population of uncertain size, it is not always possible to reliably estimate their frequency or establish a causal relationship to drug exposure.

Body as a Whole

Redistribution/accumulation of body fat.

Endocrine and Metabolic

Hyperglycemia.

General

Weakness.

Hemic and Lymphatic

Anemia (including pure red cell aplasia, sideroblastic anemia, and severe anemias progressing on therapy).

Hepatic and Pancreatic

Lactic acidosis and hepatic steatosis, pancreatitis, posttreatment exacerbations of HBV [see Warnings and Precautions (5.1, 5.4)].

Hepatobiliary Disorders

Acute liver failure, hepatotoxicity.

Hypersensitivity

Anaphylaxis, urticaria.

Investigations

Weight increased.

Musculoskeletal

Arthralgia, creatinine phosphokinase (CPK) elevation, muscle weakness, myalgia, rhabdomyolysis.

Nervous System

Paresthesia, peripheral neuropathy.

Skin

Alopecia.

7 DRUG INTERACTIONS

7.1 Coadministration with Other Antiretroviral Drugs

DOVATO is a complete regimen for the treatment of HIV-1 infection; therefore, coadministration with other antiretroviral drugs for the treatment of HIV-1 infection is not recommended [see Indications and Usage (1)]. Information regarding potential drug-drug interactions with other antiretroviral drugs is not provided [see Contraindications (4), Warnings and Precautions (5.5), Clinical Pharmacology (12.3)].

7.2 Potential for DOVATO to Affect Other Drugs

Dolutegravir, a component of DOVATO, inhibits the renal organic cation transporters (OCT)2 and multidrug and toxin extrusion transporter (MATE)1; thus, it may increase plasma concentrations of drugs eliminated via OCT2 or MATE1 such as dofetilide, dalfampridine, and metformin [see Contraindications (4), Drug Interactions (7.4), Clinical Pharmacology (12.3)].

7.3 Potential for Other Drugs to Affect the Components of DOVATO

Dolutegravir is metabolized by uridine diphosphate (UDP)-glucuronosyl transferase (UGT)1A1 with some contribution from cytochrome P450 (CYP)3A. Dolutegravir is also a substrate of UGT1A3, UGT1A9, breast cancer resistance protein (BCRP), and P-glycoprotein (P-gp) in vitro. Drugs that induce those enzymes and transporters may decrease dolutegravir plasma concentrations and reduce the therapeutic effect of DOVATO [see Drug Interactions (7.4), Clinical Pharmacology (12.3)]. Coadministration of DOVATO and other drugs that inhibit these enzymes may increase dolutegravir plasma concentrations.

Coadministration of dolutegravir with polyvalent cation-containing products may lead to decreased absorption of dolutegravir [see Drug Interactions (7.4), Clinical Pharmacology (12.3)].

7.4 Established and Other Potentially Significant Drug Interactions

No drug interaction studies were conducted with DOVATO. The drug interactions described are based on studies conducted with dolutegravir or lamivudine when administered alone [see Clinical Pharmacology (12.3)]. Information regarding potential drug interactions with DOVATO are provided in Table 5. These recommendations are based on either drug interaction trials or predicted interactions due to the expected magnitude of interaction and potential for serious adverse events or loss of efficacy [see Contraindications (4), Clinical Pharmacology (12.3)].

Table 5. Established and Other Potentially Significant Drug Interactions for DOVATO: Alterations in Dose May Be Recommended Based on Drug Interaction Trials or Predicted Interactions
Coadministered Drug Class:; Drug Name | Effect on Concentration | Clinical Comment
Antiarrhythmic:; Dofetilide | ↑Dofetilide | Coadministration is contraindicated with DOVATO [see Contraindications (4)].
Anticonvulsant:; Carbamazepinea | ↓Dolutegravir | An additional dolutegravir 50-mg dose should be taken, separated by 12 hours from DOVATO [see Dosage and Administration (2.3)].
Anticonvulsants:; Oxcarbazepine; Phenytoin Phenobarbital | ↓Dolutegravir | Avoid coadministration with DOVATO because there are insufficient data to make dosing recommendations.
Antidiabetic:; Metformina | ↑Metformin | Refer to the prescribing information for metformin for assessing the benefit and risk of concomitant use of DOVATO and metformin.
Antimycobacterial:; Rifampina | ↓Dolutegravir | An additional 50-mg dose of dolutegravir should be taken, separated by 12 hours from DOVATO [see Dosage and Administration (2.3)].
Herbal product:; St. John’s wort (Hypericum perforatum) | ↓Dolutegravir | Avoid coadministration with DOVATO because there are insufficient data to make dosing recommendations.
Medications containing polyvalent cations; (e.g., Mg or Al):; Cation-containing antacidsa or laxatives; Sucralfate; Buffered medications | ↓Dolutegravir | Administer DOVATO 2 hours before or 6 hours after taking medications containing polyvalent cations.
Oral calcium and iron supplements, including multivitamins containing calcium or irona | ↓Dolutegravir | When taken with food, DOVATO and supplements or multivitamins containing calcium or iron can be taken at the same time. Under fasting conditions, DOVATO should be taken 2 hours before or 6 hours after taking supplements containing calcium or iron.
Potassium channel blocker:; Dalfampridine | ↑Dalfampridine | Elevated levels of dalfampridine increase the risk of seizures. The potential benefits of taking dalfampridine concurrently with DOVATO should be considered against the risk of seizures in these patients.
Sorbitola | ↓Lamivudine | When possible, avoid use of sorbitol-containing medicines with DOVATO.
↑ = Increase, ↓ = Decrease.
a See Clinical Pharmacology (12.3) Table 8 or Table 9 for magnitude of interaction.

8 USE IN SPECIFIC POPULATIONS

8.1 Pregnancy

Pregnancy Exposure Registry

There is a pregnancy exposure registry that monitors pregnancy outcomes in individuals exposed to DOVATO during pregnancy. Healthcare providers are encouraged to register patients by calling the Antiretroviral Pregnancy Registry (APR) at 1‑800‑258‑4263.

Risk Summary

Data from two, ongoing birth outcome surveillance studies in Botswana and Eswatini which together include over 14,000 individuals evaluated during pregnancy show similar prevalence of neural tube defects among infants born to individuals taking dolutegravir at the time of conception compared to those born to individuals taking non-dolutegravir-containing regimens at conception or infants born to HIV-negative individuals (see Data).

There are insufficient human data on the use of DOVATO during pregnancy to definitively assess a drug-associated risk for birth defects and miscarriage. However, available human data from the APR with the individual components of DOVATO do not indicate an increased risk of birth defects (see Data). The background risk for major birth defects for the indicated population is unknown. In the U.S. general population, the estimated background rate for major birth defects and miscarriage in clinically recognized pregnancies is 2% to 4% and 15% to 20%, respectively.

In animal reproduction studies, no evidence of adverse developmental outcomes (including neural tube defects) was observed with dolutegravir at systemic exposures (AUC) less than (rabbits) and 50 times (rats) the exposure in humans at the recommended human dose (RHD) (see Data). Oral administration of lamivudine to pregnant rabbits during organogenesis resulted in embryolethality at systemic exposure (AUC) similar to the RHD; however, no adverse developmental effects were observed with oral administration of lamivudine to pregnant rats during organogenesis at plasma concentrations (Cmax) 35 times the RHD (see Data).

Data

Human Data:

Dolutegravir:

Observational studies: The first interim analysis from an ongoing birth outcome surveillance study in Botswana identified an association between dolutegravir and an increased risk of neural tube defects when dolutegravir was administered at the time of conception and in early pregnancy. A subsequent analysis was conducted based on a larger cohort from the birth outcome surveillance study in Botswana and included over 9,460 individuals exposed to dolutegravir at conception, 23,664 individuals exposed to non-dolutegravir-containing regimens, and 170,723 HIV-negative pregnant individuals. The prevalence of neural tube defects in infants delivered to individuals taking dolutegravir at conception was 0.11% (95% CI: 0.05-0.19%). The observed prevalence rate did not differ significantly from that of infants delivered to individuals taking non-dolutegravir-containing regimens (0.11%, 95% CI: 0.07-0.16%), or to HIV-negative individuals (0.06%, 95% CI: 0.05-0.08%).

The Eswatini birth outcome surveillance study includes 9,743 individuals exposed to dolutegravir at conception, 1,838 individuals exposed to non-dolutegravir-containing regimens, and 32,259 HIV-negative pregnant individuals. The prevalence of neural tube defects in infants delivered to individuals taking dolutegravir at conception was 0.08% (95% CI: 0.04-0.16%). The observed prevalence rate did not differ significantly from that of infants delivered to individuals taking non-dolutegravir-containing regimens (0.22%, 95% CI: 0.06-0.56%) or to HIV-negative individuals (0.08%, 95% CI: 0.06-0.12%). The observed prevalence of neural tube defects in infants delivered to individuals taking non-dolutegravir-containing regimens had a wide confidence interval due to low sample size.

Limitations of these birth outcome surveillance studies include insufficient data to determine if baseline characteristics were balanced between the study groups or to assess other factors such as the use of folic acid during the preconception or first trimester periods.

Antiretroviral Pregnancy Registry:

Based on prospective reports to the APR, of 1,377 exposures to dolutegravir during pregnancy resulting in live births (including 874 exposed in the first trimester), the prevalence of defects in live births was 3.3% (95% CI: 2.2% to 4.7%) following first-trimester exposure to dolutegravir-containing regimens and 5.0% (95% CI: 3.2% to 7.3%) following second-/third-trimester exposure to dolutegravir-containing regimens. In the U.S. reference population of the Metropolitan Atlanta Congenital Defects Program (MACDP), the background birth defect rate was 2.7%.

Dolutegravir has been shown to cross the placenta. In a clinical trial in Uganda and South Africa in women during the last trimester of pregnancy receiving dolutegravir 50 mg once daily, the ratio of median dolutegravir concentration in fetal umbilical cord to that in maternal peripheral plasma was 1.21 (range 0.51 to 2.11) (n = 15).

Lamivudine: Based on prospective reports to the APR of exposures to lamivudine during pregnancy resulting in live births (including over 5,600 exposed in the first trimester and over 7,500 exposed in the second/third trimester), there was no difference between the overall risk of birth defects for lamivudine compared with the background birth defect rate of 2.7% in the U.S. reference population of the MACDP. The prevalence of defects in live births was 3.1% (95% CI: 2.6% to 3.6%) following first trimester exposure to lamivudine-containing regimens and 2.9% (95% CI: 2.5% to 3.3%) following second/third trimester exposure to lamivudine-containing regimens.

Lamivudine pharmacokinetics were studied in pregnant women during 2 clinical trials conducted in South Africa. The trials assessed pharmacokinetics in 16 women at 36 weeks’ gestation using lamivudine 150 mg twice daily with zidovudine, 10 women at 38 weeks’ gestation using lamivudine 150 mg twice daily with zidovudine, and 10 women at 38 weeks’ gestation using lamivudine 300 mg twice daily without other antiretrovirals. These trials were not designed or powered to provide efficacy information. Lamivudine concentrations were generally similar in maternal, neonatal, and umbilical cord serum samples. In a subset of subjects, amniotic fluid specimens were collected following natural rupture of membranes and confirmed that lamivudine crosses the placenta in humans. Based on limited data at delivery, median (range) amniotic fluid concentrations of lamivudine were 3.9-fold (1.2- to 12.8-fold) greater compared with paired maternal serum concentration (n = 8).

Animal Data:

Dolutegravir: Dolutegravir was administered orally to pregnant rats and rabbits (up to 1,000 mg/kg/day) on Gestation Days 6 to 17 and 6 to 18, respectively, and also to rats on Gestation Day 6 to Lactation/Postpartum Day 20. No adverse effects on embryo-fetal (rats and rabbits) or pre/postnatal (rats) development were observed up to the highest dose tested. During organogenesis, systemic exposures (AUC) to dolutegravir in rabbits were less than the exposure in humans at the RHD and in rats were approximately 50 times the exposure in humans at the RHD. In the rat pre/postnatal development study, decreased body weight of the developing offspring was observed during lactation at a maternally toxic dose (approximately 50 times human exposure at the RHD).

Lamivudine: Lamivudine was administered orally to pregnant rats (at 90, 600, and 4,000 mg/kg/day) and rabbits (at 90, 300 and 1,000 mg/kg/day and at 15, 40, and 90 mg/kg/day) during organogenesis (on Gestation Days 7 through 16 [rat] and 8 through 20 [rabbit]). No evidence of fetal malformations due to lamivudine was observed in rats and rabbits at doses producing plasma concentrations (Cmax) approximately 35 times higher than human exposure at the RHD. Evidence of early embryolethality was seen in the rabbit at systemic exposures (AUC) similar to those observed in humans, but there was no indication of this effect in the rat at plasma concentrations (Cmax) 35 times higher than human exposure at the RHD. Studies in pregnant rats showed that lamivudine is transferred to the fetus through the placenta. In the fertility/pre- and postnatal development study in rats, lamivudine was administered orally at doses of 180, 900, and 4,000 mg/kg/day (from prior to mating through Postnatal Day 20). In the study, development of the offspring, including fertility and reproductive performance, was not affected by the maternal administration of lamivudine.

8.2 Lactation

Risk Summary

Dolutegravir and lamivudine are present in human milk. There is no information on the effects of DOVATO or the components of DOVATO on the breastfed infant or the effects of the drugs on milk production.

Potential risks of breastfeeding include: (1) HIV‑1 transmission (in HIV-1–negative infants), (2) developing viral resistance (in HIV-1–positive infants), and (3) adverse reactions in a breastfed infant similar to those seen in adults.

8.4 Pediatric Use

The safety and efficacy of DOVATO for the treatment of HIV-1 infection have been established in adolescents 12 years of age and older and weighing at least 25 kg. Use of DOVATO for this indication is supported by DANCE trial in treatment-naïve adolescents and evidence from adequate and well-controlled trials in adults, GEMINI-1, GEMINI-2 (treatment-naïve adults) and TANGO (virologically-suppressed adults) [see Adverse Reactions (6.1), Clinical Pharmacology (12.3), Clinical Studies (14)]. Overall, the safety and efficacy data in adolescent subjects from the DANCE trial were comparable to those observed in adults, and there was no clinically significant difference in exposure for the components of DOVATO [see Adverse Reactions (6.1), Clinical Pharmacology (12.3), Clinical Studies (14.4)].

The safety and efficacy of DOVATO have not been established in pediatric patients less than 12 years of age or weighing less than 25 kg.

8.5 Geriatric Use

Clinical trials of DOVATO did not include sufficient numbers of subjects aged 65 and over to determine whether they respond differently from younger subjects. In general, caution should be exercised in the administration of DOVATO in elderly patients reflecting the greater frequency of decreased hepatic, renal, or cardiac function, and of concomitant disease or other drug therapy [see Clinical Pharmacology (12.3)].

8.6 Renal Impairment

DOVATO is not recommended for patients with creatinine clearance <30 mL/min because DOVATO is a fixed-dose combination, and the dosage of the individual components cannot be adjusted. If a dose reduction of lamivudine, a component of DOVATO, is required for patients with creatinine clearance <30 mL/min, then the individual components should be used.

Patients with a creatinine clearance between 30 and 49 mL/min receiving DOVATO may experience a 1.6- to 3.3-fold higher lamivudine exposure (AUC) than patients with a creatinine clearance ≥50 mL/min. There are no safety data from randomized, controlled trials comparing DOVATO to the individual components in patients with a creatinine clearance between 30 and 49 mL/min who received dose-adjusted lamivudine. In the original lamivudine registrational trials in combination with zidovudine, higher lamivudine exposures were associated with higher rates of hematologic toxicities (neutropenia and anemia), although discontinuations due to neutropenia or anemia each occurred in <1% of subjects. Patients with a sustained creatinine clearance between 30 and 49 mL/min who receive DOVATO should be monitored for hematologic toxicities. If new or worsening neutropenia or anemia develop, dose adjustment of lamivudine, per lamivudine prescribing information, is recommended. If lamivudine dose adjustment is indicated, DOVATO should be discontinued, and the individual components should be used to construct the treatment regimen.

8.7 Hepatic Impairment

No dosage adjustment of DOVATO is necessary in patients with mild or moderate hepatic impairment (Child-Pugh Score A or B). Dolutegravir has not been studied in patients with severe hepatic impairment (Child-Pugh Score C); therefore, DOVATO is not recommended for patients with severe hepatic impairment.

10 OVERDOSAGE

There is no known specific treatment for overdose with DOVATO. If overdose occurs, the patient should be monitored, and standard supportive treatment applied as required.

Dolutegravir

As dolutegravir is highly bound to plasma proteins, it is unlikely that it will be significantly removed by dialysis.

Lamivudine

Because a negligible amount of lamivudine was removed via (4-hour) hemodialysis, continuous ambulatory peritoneal dialysis, and automated peritoneal dialysis, it is not known if continuous hemodialysis would provide clinical benefit in a lamivudine overdose event.

11 DESCRIPTION

DOVATO is a fixed-dose combination tablet containing dolutegravir (as dolutegravir sodium), an integrase strand transfer inhibitor (INSTI), and lamivudine (also known as 3TC), a nucleoside analogue reverse transcriptase inhibitor (NRTI).

DOVATO tablets are for oral administration. Each film-coated tablet contains the active ingredients 50 mg of dolutegravir (equivalent to 52.6 mg dolutegravir sodium) and 300 mg of lamivudine and the inactive ingredients magnesium stearate, mannitol, microcrystalline cellulose, povidone K29/32, sodium starch glycolate, sodium stearyl fumarate. The tablet film-coating contains the inactive ingredients hypromellose, polyethylene glycol, titanium dioxide.

Dolutegravir

The chemical name of dolutegravir sodium is sodium (4R,12aS)-9-{[(2,4-difluorophenyl)methyl]carbamoyl}-4-methyl-6,8-dioxo-3,4,6,8,12,12a-hexahydro-2H-pyrido[1',2':4,5]pyrazino[2,1-b][1,3]oxazin-7-olate. The empirical formula is C20H18F2N3NaO5, and the molecular weight is 441.36 g/mol. It has the following structural formula:

Dolutegravir sodium is a white to light yellow powder and is slightly soluble in water.

Lamivudine

The chemical name of lamivudine is (2R,cis)-4-amino-1-(2-hydroxymethyl-1,3-oxathiolan-5-yl)-(1H)-pyrimidin-2-one. Lamivudine is the (‑)enantiomer of a dideoxy analogue of cytidine. Lamivudine has also been referred to as (‑)2′,3′-dideoxy, 3′-thiacytidine. It has a molecular formula of C8H11N3O3S and a molecular weight of 229.3 g/mol. It has the following structural formula:

Lamivudine is a white to off‑white crystalline solid and is soluble in water.

12 CLINICAL PHARMACOLOGY

12.1 Mechanism of Action

DOVATO is a fixed-dose combination of the HIV‑1 antiretroviral agents, dolutegravir and lamivudine [see Microbiology (12.4)].

12.2 Pharmacodynamics

Cardiac Electrophysiology

The effect of combination therapy as DOVATO or lamivudine given alone on the QT interval has not been studied. At a 250-mg suspension dose (exposures approximately 3-fold that of the 50-mg once-daily dose at steady state), dolutegravir given alone did not prolong the QTc interval to any clinically relevant extent.

Effects of Dolutegravir on Renal Function

No clinically significant dolutegravir exposure-response relationship on the glomerular filtration rate or effective renal plasma flow was observed. The effect of dolutegravir on renal function was evaluated in an open-label, randomized, 3-arm, parallel, placebo-controlled trial in healthy subjects (n = 37) who received dolutegravir 50 mg once daily (n = 12), dolutegravir 50 mg twice daily (n = 13), or placebo once daily (n = 12) for 14 days.

12.3 Pharmacokinetics

The Cmax, Ctrough, and AUCtau parameters of the components of DOVATO are provided in Table 6.

Table 6. Multiple-Dose Pharmacokinetic Parameters of the Components of DOVATO
Parameter Mean (%CV) | Dolutegravira | Lamivudineb
Cmax (mcg/mL) | 3.67 (20%) | 2.04 (26%)
Ctrough (mcg/mL) | 1.11 (46%) | 0.042 (38%)
AUCtau (mcg·h/mL) | 53.6 (27%) | 8.87 (21%)
Cmax = Maximum concentration; Ctrough = Lowest concentration before administration of the next dose; AUCtau = Area under the concentration-time curve integrated across the dosing interval.
a Based on dolutegravir 50-mg once-daily dosage administered to antiretroviral treatment-naive adults.
b Based on lamivudine 300-mg once-daily dosage administered to healthy subjects.

The absorption, distribution, and elimination pharmacokinetic parameters of the components of DOVATO are provided in Table 7.

Table 7. Pharmacokinetic Properties of the Components of DOVATO
Pharmacokinetic Parameters | Dolutegravir | Lamivudine
Absorption
Tmax (h), mediana | 2.5 | 1
Effect of Food
High-fat mealb (relative to fasting) | No clinically significant differences in the pharmacokinetics of either component (after administration of DOVATO) were observedc.
Distribution
Plasma protein bindingd | Approximately 99% | 36%
Blood-to-plasma ratio | 0.44 - 0.54 | 1.1 - 1.2
Elimination
t1/2 (h) | Approximately 14 | 13 - 19
Metabolism
Metabolic pathways | UGT1A1 (primary); CYP3A (minor) | Not significantly metabolized
Excretion
Major route of elimination | Metabolism | Renal, by OCT system
Urine (unchanged) | 31% (<1%)e | Approximately 70%f
Feces (unchanged) | 64% (53%)e | −
Tmax = Time to maximum concentration (Cmax); t1/2 = Elimination half-life; UGT = Uridine diphosphate glucuronosyl transferase; CYP = Cytochrome P450; OCT = Organic cation transporter.
a After administration of DOVATO (fasted state).
b High-fat meal is approximately 900 kcal, 56% fat.
c The geometric mean (90% confidence interval) AUC ratio (fed/fasted) of dolutegravir and lamivudine is 1.33 (1.18, 1.48) and 0.91 (0.87, 0.96), respectively.
d Based on in vitro data.
e Based on single-dose, mass balance study of radiolabeled dolutegravir.
f Based on 24-hour urine collection obtained after oral or IV administration.

Specific Populations

No clinically significant differences in the pharmacokinetics of the components of DOVATO were observed based on age, sex, or race. Pharmacokinetic data for dolutegravir and lamivudine in subjects 65 years of age and older are limited.

Patients with Renal Impairment: The pharmacokinetics for the individual components of DOVATO have been evaluated in patients with renal impairment. See the U.S. prescribing information for the individual components, TIVICAY (dolutegravir) and EPIVIR (lamivudine).

Patients with Hepatic Impairment: The pharmacokinetics for the individual components of DOVATO have been evaluated in patients with varying degrees of hepatic impairment. See the U.S. prescribing information for the individual components, TIVICAY (dolutegravir) and EPIVIR (lamivudine).

Pediatric Subjects: In adolescents receiving DOVATO, dolutegravir and lamivudine exposures were higher as compared to adults; however, the differences in exposure were not considered clinically significant. Lamivudine and dolutegravir exposures were within the observed ranges at the recommended doses in adults and pediatrics receiving the individual components of DOVATO (Table 8).

Table 8. Pharmacokinetic Parameters Following Dovato in Adolescent Subjects 12 to Less than 18 Years of Age Weighing at Least 25 kg (n = 32)
Age/weight | Dose | Pharmacokinetic Parameter Estimates Geometric Mean (CV%)
Age/weight | Dose | AUC(0-24) mcg·h/mL | Cmax mcg/mL | C24 mcg/mL
12 to <18 years of age and ≥25 kg | Dolutegravir; 50 mg once daily | 78.2 (91.6) | 6.71 (69.5) | 1.46 (154)
12 to <18 years of age and ≥25 kg | Lamivudine; 300 mg once daily | 14.7 (112) | 2.95 (82.8) | 0.106 (312)

Pregnant women: Lamivudine: Lamivudine pharmacokinetics were studied in 36 pregnant women during 2 clinical trials conducted in South Africa. Lamivudine pharmacokinetics in pregnant women were similar to those seen in non-pregnant adults and in postpartum women. Lamivudine concentrations were generally similar in maternal, neonatal, and umbilical cord serum samples.

Drug Interaction Studies

Clinical Studies: No drug interaction studies were conducted with DOVATO. The drug interaction studies described below were conducted with dolutegravir or lamivudine when used alone. Table 9 summarizes the effects of dolutegravir on the pharmacokinetics of coadministered drugs. Table 10 summarizes the effect of other drugs on the pharmacokinetics of dolutegravir when used alone and Table 11 summarizes the effect of sorbitol on the pharmacokinetics of lamivudine when used alone.

Table 9. Effect of Dolutegravir on the Pharmacokinetics of Coadministered Drugs
Coadministered Drug(s); and Dose(s) | Dose of Dolutegravir | Geometric Mean Ratio (90% CI) of Pharmacokinetic Parameters of Coadministered Drug with/without Dolutegravir No Effect = 1.00
Coadministered Drug(s); and Dose(s) | Dose of Dolutegravir | Cmax | AUC | Ctau or C24
Ethinyl estradiol; 0.035 mg | 50 mg; twice daily | 0.99; (0.91 to 1.08) | 1.03; (0.96 to 1.11) | 1.02; (0.93 to 1.11)
Grazoprevir; 200 mg once daily | 50 mg; single dose | 0.64; (0.44, 0.93) | 0.81; (0.67, 0.97) | 0.86; (0.79, 0.93)
Metformina; 500 mg twice daily | 50 mg; once daily | 1.66; (1.53 to 1.81) | 1.79; (1.65 to 1.93) | _
Metformina; 500 mg twice daily | 50 mg; twice daily | 2.11; (1.91 to 2.33) | 2.45; (2.25 to 2.66) | _
Methadone; 16 to 150 mg | 50 mg; twice daily | 1.00; (0. 94 to 1.06) | 0.98; (0.91 to 1.06) | 0.99; (0.91 to 1.07)
Midazolam; 3 mg | 25 mg; once daily | _ | 0.95; (0.79 to 1.15) | _
Norelgestrominb; 0.25 mg | 50 mg; twice daily | 0.89; (0.82 to 0.97) | 0.98; (0.91 to 1.04) | 0.93; (0.85 to 1.03)
Sofosbuvir; 400 mg once daily; Metabolite (GS-331007) | 50 mg; once daily | 0.88; (0.80, 0.98); 1.01; (0.93, 1.10) | 0.92; (0.85, 0.99); 0.99; (0.97, 1.01) | NA; 0.99; (0.97, 1.01)
Velpatasvir; 100 mg once daily | 50 mg; once daily | 0.94; (0.86, 1.02) | 0.91; (0.84, 0.98) | 0.88; (0.82, 0.94)
a Organic cation transporter (OCT)2 or multidrug and toxin extrusion (MATE)1 substrate.
b Norelgestromin is the active metabolite of norgestimate.

No clinically significant differences in the pharmacokinetics of tenofovir (organic anion transporter [OAT]1 and OAT3 substrates) or para-amino hippurate (OAT1 and OAT3 substrates) were observed when coadministered with dolutegravir.

No clinically significant differences in the pharmacokinetics of trimethoprim/sulfamethoxazole were observed when coadministered with lamivudine.

Table 10. Effect of Coadministered Drugs on the Pharmacokinetics of Dolutegravir
Coadministered Drug(s); and Dose(s) | Dose of Dolutegravir | Geometric Mean Ratio (90% CI) of Dolutegravir Pharmacokinetic Parameters with/without Coadministered Drugs No Effect = 1.00
Coadministered Drug(s); and Dose(s) | Dose of Dolutegravir | Cmax | AUC | Cτau or C24
Antacid (MAALOX); simultaneous administration | 50-mg; single dose | 0.28; (0.23 to 0.33) | 0.26; (0.22 to 0.32) | 0.26; (0.21 to 0.31)
Antacid (MAALOX); 2 h after dolutegravir | 50-mg; single dose | 0.82; (0.69 to 0.98) | 0.74; (0.62 to 0.90) | 0.70; (0.58 to 0.85)
Calcium carbonate 1,200 mg; simultaneous administration (fasted) | 50-mg; single dose | 0.63; (0.50 to 0.81) | 0.61; (0.47 to 0.80) | 0.61; (0.47 to 0.80)
Calcium carbonate 1,200 mg; simultaneous administration (fed) | 50-mg; single dose | 1.07; (0.83 to 1.38) | 1.09; (0.84 to 1.43) | 1.08; (0.81 to 1.42)
Calcium carbonate 1,200 mg; 2 h after dolutegravir | 50-mg; single dose | 1.00; (0.78 to 1.29) | 0.94; (0.72 to 1.23) | 0.90; (0.68 to 1.19)
Carbamazepine; 300 mg twice daily | 50 mg; once daily | 0.67; (0.61 to 0.73) | 0.51; (0.48 to 0.55) | 0.27; (0.24 to 0.31)
Ferrous fumarate 324 mg; simultaneous administration (fasted) | 50-mg; single dose | 0.43; (0.35 to 0.52) | 0.46; (0.38 to 0.56) | 0.44; (0.36 to 0.54)
Ferrous fumarate 324 mg; simultaneous administration (fed) | 50-mg; single dose | 1.03; (0.84 to 1.26) | 0.98; (0.81 to 1.20) | 1.00; (0.81 to 1.23)
Ferrous fumarate 324 mg; 2 h after dolutegravir | 50-mg; single dose | 0.99; (0.81 to 1.21) | 0.95; (0.77 to 1.15) | 0.92; (0.74 to 1.13)
Multivitamin (One-A-Day); simultaneous administration | 50-mg; single dose | 0.65; (0.54 to 0.77) | 0.67; (0.55 to 0.81) | 0.68; (0.56 to 0.82)
Omeprazole; 40 mg once daily | 50-mg; single dose | 0.92; (0.75 to 1.11) | 0.97; (0.78 to 1.20) | 0.95; (0.75 to 1.21)
Prednisone; 60 mg once daily with taper | 50 mg; once daily | 1.06; (0.99 to 1.14) | 1.11; (1.03 to 1.20) | 1.17; (1.06 to 1.28)
Rifampina; 600 mg once daily | 50 mg; twice daily | 0.57; (0.49 to 0.65) | 0.46; (0.38 to 0.55) | 0.28; (0.23 to 0.34)
Rifampinb; 600 mg once daily | 50 mg; twice daily | 1.18; (1.03 to 1.37) | 1.33; (1.15 to 1.53) | 1.22; (1.01 to 1.48)
Rifabutin; 300 mg once daily | 50 mg; once daily | 1.16; (0.98 to 1.37) | 0.95; (0.82 to 1.10) | 0.70; (0.57 to 0.87)
a Comparison is rifampin taken with dolutegravir 50 mg twice daily compared with dolutegravir 50 mg twice daily.
b Comparison is rifampin taken with dolutegravir 50 mg twice daily compared with dolutegravir 50 mg once daily.

Table 11. Effect of Sorbitol on the Pharmacokinetics of Lamivudine
Coadministered Drug and Dosea |  | Lamivudine Pharmacokinetic Parameters; (% Decreased)
Coadministered Drug and Dosea |  | Cmax | AUC0-24 | AUCinf
Sorbitol (Excipient) | 3.2 grams | 28% | 20% | 14%
Sorbitol (Excipient) | 10.2 grams | 52% | 39% | 32%
Sorbitol (Excipient) | 13.4 grams | 55% | 44% | 36%
Cmax = Maximum concentration; AUC(0-24) = Area under the concentration-time curve integrated from time of administration to 24 hours; AUC(inf) = Area under the concentration-time curve from the time of administration to infinity.
a Coadministered with a single dose of lamivudine 300 mg.

No clinically significant differences in the pharmacokinetics of lamivudine were observed when coadministered with trimethoprim (MATE1, MATE2-K, and OCT2 inhibitor)/sulfamethoxazole, interferon alfa, or ribavirin.

In Vitro Studies Where Drug Interaction Potential Was Not Further Evaluated Clinically: Dolutegravir: Dolutegravir does not inhibit CYP1A2, CYP2A6, CYP2B6, CYP2C8, CYP2C9, CYP2C19, CYP2D6, or CYP3A. Dolutegravir does not induce CYP1A2, CYP2B6, or CYP3A4.

Dolutegravir is a substrate of UGT1A3 and UGT1A9. Dolutegravir does not inhibit UGT1A1 or UGT2B7.

Dolutegravir is a substrate of BCRP and P-gp. Dolutegravir does not inhibit P‑gp, BCRP, bile salt export pump (BSEP), organic anion transporter polypeptide (OATP)1B1, OATP1B3, OCT1, multidrug resistance protein (MRP)2, or MRP4. Dolutegravir is not a substrate of OATP1B1 or OATP1B3.

Lamivudine: Lamivudine is a substrate of P-gp and BCRP. Lamivudine does not inhibit OATP1B1/3, BCRP, P-gp, MATE1, MATE2-K, OCT1, OCT2, or OCT3.

12.4 Microbiology

Mechanism of Action

Dolutegravir: Dolutegravir inhibits HIV integrase by binding to the integrase active site and blocking the strand transfer step of retroviral DNA integration which is essential for the HIV replication cycle. Strand transfer biochemical assays using purified recombinant HIV‑1 integrase and pre-processed substrate DNA resulted in IC50 values of 2.7 nM and 12.6 nM.

Lamivudine: Lamivudine is a synthetic nucleoside analogue. Intracellularly lamivudine is phosphorylated to its active 5′-triphosphate metabolite, lamivudine triphosphate (3TC‑TP). The principal mode of action of 3TC‑TP is inhibition of reverse transcriptase (RT) via DNA chain termination after incorporation of the nucleotide analogue.

Antiviral Activity in Cell Culture

Dolutegravir: Dolutegravir exhibited antiviral activity against laboratory strains of wild-type HIV‑1 with mean concentrations of drug necessary to affect viral replication by 50 percent (EC50) values of 0.5 nM (0.21 ng/mL) to 2.1 nM (0.85 ng/mL) in peripheral blood mononuclear cells (PBMCs) and MT-4 cells.

Dolutegravir exhibited antiviral activity against 13 clinically diverse clade B isolates with a mean EC50 value of 0.52 nM in a viral integrase susceptibility assay using the integrase coding region from clinical isolates. Dolutegravir demonstrated antiviral activity in cell culture against a panel of HIV-1 clinical isolates (3 in each group of M [clades A to G], and 3 in group O) with EC50 values ranging from 0.02 nM to 2.14 nM for HIV-1. Dolutegravir EC50 values against three HIV-2 clinical isolates in PBMC assays ranged from 0.09 nM to 0.61 nM.

Lamivudine: The antiviral activity of lamivudine against HIV‑1 was assessed in a number of cell lines including monocytes and PBMCs using standard susceptibility assays. EC50 values were in the range of 3 to 15,000 nM (1 nM = 0.23 ng/mL). The EC50 values of lamivudine against different HIV-1 clades (A-G) and group O viruses ranged from 1 to 120 nM, and against HIV-2 isolates from 3 to 120 nM in PBMCs.

Antiviral Activity in Combination with Other Antiviral Agents

Neither dolutegravir nor lamivudine were antagonistic to all tested anti-HIV agents.

Resistance

Cell Culture: Dolutegravir: Dolutegravir-resistant viruses were selected in cell culture starting from different wild-type HIV‑1 strains and clades. Amino acid substitutions emerged in different passages; the substitution G118R emergence conferred decreased susceptibility to dolutegravir of 10-fold, while substitutions E92Q, S153F or Y, G193E, or R263K conferred decreased susceptibility to dolutegravir of up to 4-fold.

Lamivudine: HIV-1 resistance to lamivudine involves the development of a M184V or M184I amino acid change close to the active site of the viral RT. This variant arises both in cell culture and in HIV-1–infected patients treated with lamivudine-containing antiretroviral therapy. Substitutions M184V or I confer high-level resistance to lamivudine.

Clinical Subjects: At Week 144, none of the 12 subjects in the dolutegravir plus lamivudine group or the 9 subjects in the dolutegravir plus TDF/FTC group who met the protocol-defined confirmed virologic withdrawal criteria across the pooled GEMINI-1 and GEMINI-2 trials had emergent INSTI- or NRTI-resistance substitutions.

No subject who received DOVATO in the TANGO trial met the protocol-defined confirmed virologic withdrawal criteria through Week 144. No emergent INSTI- or NRTI-resistance was detected by genotypic or phenotypic analyses of the last on-treatment isolate from one subject who received DOVATO with HIV-1 RNA ≥400 copies/mL at withdrawal. No emergent resistance was detected by genotypic or phenotypic analyses of HIV-1 integrase, protease, or reverse transcriptase at the time of virologic failure in 3 subjects in the TBR arm who met the confirmed virologic withdrawal criteria.

Cross-Resistance

Dolutegravir: The susceptibility of dolutegravir was tested against 60 INSTI-resistant site-directed mutant HIV-1 viruses (28 with single substitutions and 32 with 2 or more substitutions). The single INSTI-resistance substitutions T66K, I151L, and S153Y conferred a >2-fold decrease in dolutegravir susceptibility (range: 2.3-fold to 3.6-fold from reference). Combinations of multiple substitutions T66K/L74M; E92Q/N155H; G140C/Q148R; G140S/Q148H, R or K; Q148R/N155H; T97A/G140S/Q148, and substitutions at E138/G140/Q148 showed a >2-fold decrease in dolutegravir susceptibility (range: 2.5-fold to 21-fold from reference).

Lamivudine: Cross-resistance conferred by the M184V or I RT has been observed within the NRTI class of antiretroviral agents. The M184V or I substitution confers resistance to emtricitabine and to abacavir, which selects M184V or I plus additional RT substitutions K65R, L74V, and Y115F. Zidovudine maintains its antiretroviral activities against lamivudine-resistant HIV-1. Abacavir and tenofovir maintain antiretroviral activity against lamivudine-resistant HIV-1 harboring only the M184V or I substitution.

13 NONCLINICAL TOXICOLOGY

13.1 Carcinogenesis, Mutagenesis, Impairment of Fertility

Carcinogenicity

Dolutegravir: Two-year carcinogenicity studies in mice and rats were conducted with dolutegravir. Mice were administered doses of up to 500 mg/kg, and rats were administered doses of up to 50 mg/kg. In mice, no significant increases in the incidence of drug-related neoplasms were observed at the highest doses tested, resulting in dolutegravir AUC exposures approximately 26 times higher than those in humans at the recommended dose. In rats, no increases in the incidence of drug-related neoplasms were observed at the highest dose tested, resulting in dolutegravir AUC exposures 17 times higher than those in humans at the recommended dose.

Lamivudine: Long‑term carcinogenicity studies with lamivudine in mice and rats showed no evidence of carcinogenic potential at exposures up to 12 times (mice) and 57 times (rats) the human exposures at the recommended dose.

Mutagenicity

Dolutegravir: Dolutegravir was not genotoxic in the bacterial reverse mutation assay, in a mouse lymphoma assay, or in the in vivo rodent micronucleus assay.

Lamivudine: Lamivudine was mutagenic in an L5178Y mouse lymphoma assay and clastogenic in a cytogenetic assay using cultured human lymphocytes. Lamivudine was not mutagenic in a microbial mutagenicity assay, in an in vitro cell transformation assay, in a rat micronucleus test, in a rat bone marrow cytogenetic assay, and in an assay for unscheduled DNA synthesis in rat liver.

Impairment of Fertility

Dolutegravir or lamivudine did not affect male or female fertility in rats at doses associated with exposures approximately 44 or 112 times, respectively, higher than the exposures in humans at the recommended dose.

14 CLINICAL STUDIES

14.1 Description of Clinical Trials

The efficacy and safety of DOVATO were evaluated in the studies summarized in Table 12.

Table 12. Trials Conducted with DOVATO in HIV-1–Infected Subjects
Population | Trial | Trial Arms | Timepoint (Week)
Adults:; Treatment-naïve | GEMINI-1 [NCT02831673] GEMINI-2 [NCT02831764] | Pooled presentation; TIVICAY plus EPIVIR; (n = 716); TIVICAY plus TRUVADA (n = 717) | 144
Virologically suppressed | TANGO [NCT03446573] | DOVATO (n = 369); TBR (n = 372) | 144
Adolescents:; Treatment-naïve (12 to less than 18 years of age and weighing at least 25 kg) | DANCE [NCT03682848] | DOVATO (n = 32) | 48
TBR = Tenofovir alafenamide-based regimen.

14.2 Clinical Trial Results in HIV-1–Infected Adult Subjects with No Antiretroviral Treatment History

GEMINI-1 and GEMINI-2 are identical 148-week, Phase 3, randomized, multicenter, parallel-group, non-inferiority trials. A total of 1,433 HIV-1–infected adults with no antiretroviral treatment history received treatment in the trials. Subjects were enrolled with a screening plasma HIV-1 RNA of 1,000 to ≤500,000 copies/mL and without evidence of major resistance-associated mutations or evidence of HBV infection. Subjects were randomized to receive a 2-drug regimen of TIVICAY 50 mg plus EPIVIR 300 mg administered once daily or TIVICAY 50 mg plus fixed-dose TRUVADA administered once daily. The primary efficacy endpoint for each GEMINI trial was the proportion of subjects with plasma HIV-1 RNA <50 copies/mL at Week 48 (Snapshot algorithm) who were randomized and treated.

At baseline, in the pooled analysis, the median age of subjects was 33 years of age, 15% female, 69% white, 9% were CDC Stage 3 (AIDS), the median plasma HIV-1 RNA was 4.4 log10 copies/mL, 20% had HIV-1 RNA >100,000 copies/mL, the median CD4^+ cell count was 432 cells/mm^3, and 8% had CD4^+ cell count ≤200 cells/mm^3; these characteristics were similar between trials and treatment arms within each trial.

Week 144 outcomes (including outcomes by key baseline covariates) for the pooled GEMINI-1 and GEMINI-2 trials are shown in Table 13. The results of the pooled analysis are consistent with the results from the individual trials, for which the secondary endpoint is the difference in proportion of subjects with plasma HIV-1 RNA <50 copies/mL at Week 144 based on the Snapshot algorithm for TIVICAY plus EPIVIR versus TIVICAY plus TRUVADA. The proportions of subjects with plasma HIV-1 RNA <50 copies/mL in the group receiving TIVICAY plus EPIVIR versus TIVICAY plus TRUVADA were 79% and 83%, respectively, in GEMINI‑1 and 84% in both treatment arms of GEMINI-2. The adjusted difference was -3.6% (95% CI: -9.4%, 2.1) for GEMINI-1 and 0.0% (95% CI: -5.3%, 5.3%) for GEMINI-2. At Week 144, no subjects who met the protocol-defined confirmed virologic withdrawal criteria had any treatment-emergent substitutions associated with resistance to dolutegravir or NRTIs.

Table 13. Pooled Virologic Outcomes of Randomized Treatment of HIV-1–Infected Adults with No Antiretroviral Treatment History in GEMINI-1 and GEMINI-2 Trials at Weeks 48 and 144 (Snapshot Algorithm)
Virologic Outcomes | GEMINI-1 and GEMINI-2 Pooled Dataa
Virologic Outcomes | Week 48 |  | Week 144
Virologic Outcomes | TIVICAY plus EPIVIR; (n = 716) | TIVICAY plus TRUVADA; (n = 717) | TIVICAY plus EPIVIR; (n = 716) | TIVICAY plus TRUVADA; (n = 717)
HIV-1 RNA <50 copies/mL | 91% | 93% | 82% | 84%
Treatment Difference (95% CI)b | -1.7% (-4.4%, 1.1%) |  | -1.8% (-5.8%, 2.1%)
Virologic nonresponse | 3% | 2% | 3% | 3%
Reasons
Data in window ≥50 copies/mL | 1% | <1% | <1% | <1%
Discontinued for lack of efficacy | <1% | <1% | 1% | <1%
Discontinued for other reasons and ≥50 copies/mL | <1% | <1% | <1% | 2%
Change in ART | <1% | <1% | <1% | <1%
No virologic data at Week 48 or Week 144 window | 6% | 5% | 15% | 14%
Reasons
Discontinued trial due to adverse event or death | 1% | 2% | 4% | 4%
Discontinued trial for other reasons | 4% | 3% | 11% | 9%
Missing data during window but on trial | <1% | 0 | <1% | <1%
Proportion (%) of Subjects with HIV-1 RNA <50 copies/mL by Baseline Category
 | % (n/N) | % (n/N) | % (n/N) | % (n/N)
Plasma Viral Load (copies/mL)
≤100,000 | 91% (526/576) | 94% (531/564) | 81% (469/576) | 84% (471/564)
>100,000 | 92% (129/140) | 90% (138/153) | 82% (115/140) | 84% (128/153)
CD4^+ (cells/mm^3)
≤200 | 79% (50/63) | 93% (51/55) | 67% (42/63) | 76% (42/55)
>200 | 93% (605/653) | 93% (618/662) | 83% (542/653) | 84% (557/662)
Gender
Male | 92% (555/603) | 94% (580/619) | 83% (500/603) | 84% (517/619)
Female | 88% (100/113) | 91% (89/98) | 74% (84/113) | 84% (82/98)
Race
White | 93% (447/480) | 95% (471/497) | 85% (409/484) | 86% (429/499)
African-American/African Heritage | 84% (83/99) | 84% (64/76) | 67% (60/90) | 73% (52/71)
Asian | 94% (67/71) | 94% (68/72) | 79% (56/71) | 82% (59/72)
Other | 88% (58/66) | 92% (66/72) | 83% (59/71) | 79% (59/75)
Ethnicity
Hispanic or Latino | 90% (193/215) | 93% (216/232) | 83% (178/215) | 85% (197/232)
Not Hispanic or Latino | 92% (462/501) | 93% (453/485) | 81% (406/501) | 83% (402/485)
Age (years)
<50 | 92% (597/651) | 94% (597/637) | 81% (530/651) | 84% (533/637)
≥50 | 89% (58/65) | 90% (72/80) | 83% (54/65) | 83% (66/80)
ART = antiretroviral treatment.
a The results of the pooled analysis are similar to the individual trials, for which the primary endpoint (proportion of subjects with plasma HIV-1 RNA <50 copies/mL at Week 48 based on the Snapshot algorithm for TIVICAY plus EPIVIR versus TIVICAY plus TRUVADA) was met. The adjusted difference was -2.6% (95% CI: -6.7%, 1.5%) for GEMINI-1 and -0.7% (95% CI: -4.3%, 2.9%) for GEMINI-2.
b Based on Cochran–Mantel–Haenszel-stratified analysis adjusting for the following baseline stratification factors: plasma HIV-1 RNA (≤100,000 copies/mL versus >100,000 copies/mL) and CD4^+ cell count (≤200 cells/mm^3 versus >200 cells/mm^3). Pooled analysis also stratified by trial. The other Snapshot outcomes (HIV-1 RNA ≥50 copies/mL and no virologic data in the visit window) were combined into a single category for the analysis.

The primary endpoint was assessed at Week 48 and the virologic success rate was 91% in the group receiving TIVICAY plus EPIVIR and 93% in the group receiving TIVICAY plus TRUVADA, with a treatment difference of -1.7% (95% CI: -4.4%, 1.1%) in the pooled data. The results of the pooled analysis are similar to the individual trials, for which the primary endpoint (proportion of subjects with plasma HIV-1 RNA <50 copies/mL at Week 48 based on the Snapshot algorithm for TIVICAY plus EPIVIR versus TIVICAY plus TRUVADA) was met. The adjusted difference was -2.6% (95% CI: ‑6.7%, 1.5%) for GEMINI-1 and -0.7% (95% CI: ‑4.3%, 2.9%) for GEMINI-2.

The adjusted mean change from baseline in CD4^+ cell count based on the pooled analysis at Week 144 was 302 cells/mm^3 for the group receiving TIVICAY plus EPIVIR and 300 cells/mm^3 for the group receiving TIVICAY plus TRUVADA.

14.3 Clinical Trial Results in HIV-1–Infected Virologically Suppressed Adult Subjects Who Switched to DOVATO

The efficacy of DOVATO in HIV-1–infected, antiretroviral treatment-experienced, virologically suppressed subjects is supported by data from a 200-week, Phase 3, randomized, open-label, multicenter, parallel-group, non-inferiority controlled trial (TANGO). A total of 741 adult HIV-1–infected subjects who were on a stable suppressive TBR received treatment in the trial. Subjects were randomized in a 1:1 ratio to receive DOVATO once daily or continue with their TBR for up to 148 weeks; at Week 148, the subjects randomized to continue with their TBR were switched to DOVATO once daily. All subjects are followed up to Week 200. Randomization was stratified by baseline third-agent class (protease inhibitor [PI], INSTI, or non-nucleoside reverse transcriptase inhibitor [NNRTI]). The primary efficacy endpoint was the proportion of subjects with plasma HIV-1 RNA ≥50 copies/mL (virologic non-response) at Week 48 (Snapshot algorithm adjusting for randomization stratification factor).

At baseline, the median age of subjects was 39 years of age, 8% were female, 21% non-white, 5% were CDC Class C (AIDS), and 98% of subjects had baseline CD4^+ cell count ≥200 cells/mm^3; these characteristics were similar between treatment arms. Subjects receiving DOVATO and a TBR had been on an antiretroviral regimen for a median of 2.8 and 2.9 years, respectively, prior to Day 1. Most subjects were on an integrase inhibitor-based TBR (78% and 80% of subjects who received DOVATO and a TBR, respectively).

In the primary 48 week analysis, <1% of subjects in both arms experienced virologic failure (HIV-1 RNA ≥50 copies/mL) at Week 48 based on the Snapshot algorithm. Based on a 4% non-inferiority margin, DOVATO was non-inferior to TBR in the primary analysis (proportion of subjects with plasma HIV-1 RNA ≥50 copies/mL), as the upper bound of the 95% CI for the adjusted treatment difference (-1.2%, 0.7%) was less than 4%.

At Week 144, the proportion of subjects with HIV-1 RNA ≥50 copies/mL (Snapshot) was 0.3% and 1.3% in the DOVATO and TBR treatment arms, respectively (Table 14).

Table 14 Virologic Outcomes of Randomized Treatment in TANGO Trial at Weeks 48 and 144 in Virologically Suppressed Subjects Who Switched to DOVATO
 | Week 48a |  | Week 144
Virologic Outcomes | DOVATO; (n = 369) | TBR; (n = 372) | DOVATO; (n = 369) | TBR; (n = 372)
Virologic nonresponse (≥50 copies/mL) | <1% | 1% | <1% | 1%
Treatment Difference (95% CI)b | -0.3% (-1.2%, 0.7%) |  | -1.1% (-2.4%, 0.2%)
HIV-1 RNA <50 copies/mLc | 93% | 93% | 86% | 82%
Reasons for virologic nonresponse
Data in window ≥50 copies/mL | 0 | 0 | 0 | 0
Discontinued for lack of efficacy | 0 | 1% | 0 | 1%
Discontinued for other reasons and ≥50 copies/mL | <1% | 0 | <1% | 0
Change in ART | 0 | 0 | 0 | <1%
Reasons for no virologic data at Week 48 or Week 144 window | 7% | 6% | 14% | 17%
Discontinued trial due to adverse event or death | 3% | <1% | 6% | 2%
Discontinued trial for other reasons | 3% | 6% | 7% | 15%
Missing data during window but on triald | 0 | <1% | 1% | 0
ART = antiretroviral treatment; TBR = Tenofovir alafenamide-based regimen.
a Based on a 4% non-inferiority margin, DOVATO is non-inferior to TBR at Week 48 in the primary analysis (proportion of subjects with plasma HIV-1 RNA ≥50 copies/mL) because the upper bound of the 95% CI for the adjusted treatment difference is less than 4%.
b Based on Cochran–Mantel–Haenszel-stratified analysis adjusting for baseline third-agent class (PI, INSTI, or NNRTI). The other Snapshot outcomes (HIV-1 RNA <50 copies/mL and no virologic data in the visit window) were combined into a single category for the analysis, and subjects who had no virologic data at Week 144 were assumed to have virologic response (<50 copies/mL).
c At Week 144 in the secondary analysis (proportion of subjects achieving plasma HIV-1 RNA <50 copies/mL), the adjusted treatment difference was 4.2% (95% CI: -1.1%, 9.5%).
d Five (5) and 2 subjects in the DOVATO and TBR arms, respectively, had no Week 144 Snapshot data due to Coronavirus Disease 2019 (COVID-19).

In TANGO, treatment outcomes between treatment arms were similar across the stratification factor, baseline third-agent class (PI, INSTI, or NNRTI), and across subgroups by age, sex, race, baseline CD4^+ cell count, CDC HIV disease stage, and countries. The median change from baseline in CD4^+ T-cell count at Week 144 was 36.0 cells/mm^3 in the DOVATO arm and 35.0 cells/mm^3 in the TBR arm.

14.4 Clinical Trial Results in Adolescent Subjects

The 48-week efficacy of DOVATO was evaluated in an open-label multicenter trial (DANCE) in 30 evaluable treatment-naïve HIV-1–infected adolescents 12 to less than18 years of age and weighing at least 25 kg. Eighty-seven percent (26/30) of subjects achieved HIV-1 RNA <50 copies/mL at Week 48, and the mean increase from baseline in CD4+ cell count was 234 cells/mm^3 at Week 48 [see Adverse Reactions (6.1), Use in Specific Populations (8.4) and Clinical Pharmacology (12.3)].

16 HOW SUPPLIED/STORAGE AND HANDLING

Each DOVATO tablet contains 50 mg of dolutegravir as dolutegravir sodium and 300 mg lamivudine and is an oval, biconvex, white, film-coated tablet, debossed with “SV 137” on one face.

Bottle of 30 tablets with child-resistant closure NDC 49702-246-13.

Blister pack of 30 tablets with child-resistant closure NDC 49702-246-33.

Store below 30°C (86°F).

17 PATIENT COUNSELING INFORMATION

Advise the patient to read the FDA-approved patient labeling (Patient Information).

Emergence of Lamivudine-Resistant HBV in Hepatitis B Co-infection

Advise all patients with HIV-1 to be tested for the presence of HBV prior to or when initiating DOVATO. Advise patients co-infected with HIV-1 and HBV that emergence of HBV variants associated with resistance to lamivudine has been reported in HIV‑1–infected subjects who have received lamivudine‑containing antiretroviral regimens. Advise patients co-infected with HIV-1 and HBV who are being treated with DOVATO to discuss with their healthcare provider if additional treatment should be considered for appropriate treatment of chronic HBV [see Warnings and Precautions (5.1)].

Severe Acute Exacerbations of Hepatitis in Patients with HBV Co-infection

Advise all patients with HIV-1 to be tested for the presence of HBV prior to or when initiating DOVATO. Advise patients co‑infected with HIV‑1 and HBV that worsening of liver disease has occurred in some cases when treatment with lamivudine was discontinued. Advise patients to discuss any changes in regimen with their healthcare provider [see Warnings and Precautions (5.1)].

Hypersensitivity Reactions

Advise patients to immediately contact their healthcare provider if they develop a rash. Instruct patients to immediately stop taking DOVATO and seek medical attention if they develop a rash associated with any of the following symptoms, as it may be a sign of a more serious reaction such as severe hypersensitivity: fever; generally ill feeling; extreme tiredness; muscle or joint aches; blisters or peeling of the skin; oral blisters or lesions; eye inflammation; facial swelling; swelling of the eyes, lips, tongue, or mouth; breathing difficulty; and/or signs and symptoms of liver problems (e.g., yellowing of the skin or whites of the eyes; dark or tea-colored urine; pale-colored stools or bowel movements; nausea; vomiting; loss of appetite; or pain, aching, or sensitivity on the right side below the ribs). Advise patients that if hypersensitivity occurs, they will be closely monitored, laboratory tests will be ordered, and appropriate therapy will be initiated [see Warnings and Precautions (5.2)].

Hepatotoxicity

Inform patients that hepatotoxicity has been reported with dolutegravir, a component of DOVATO [see Warnings and Precautions (5.3), Adverse Reactions (6.1)]. Inform patients that monitoring for hepatotoxicity during therapy with DOVATO is recommended.

Lactic Acidosis/Hepatomegaly with Steatosis

Inform patients that some HIV medicines, including DOVATO, can cause a rare, but serious condition called lactic acidosis with liver enlargement (hepatomegaly) [see Warnings and Precautions (5.4)].

Drug Interactions

DOVATO may interact with many drugs; therefore, advise patients to report to their healthcare provider the use of any other prescription or nonprescription medication or herbal products, including St. John’s wort [see Contraindications (4), Warnings and Precautions (5.5), Drug Interactions (7)].

Immune Reconstitution Syndrome

Advise patients to inform their healthcare provider immediately of any signs and symptoms of infection as inflammation from previous infection may occur soon after combination antiretroviral therapy, including DOVATO, is started [see Warnings and Precautions (5.7)].

Pregnancy Registry

Inform patients that there is an antiretroviral pregnancy registry to monitor fetal outcomes in those exposed to DOVATO during pregnancy [see Use in Specific Populations (8.1)].

Lactation

Inform individuals with HIV-1 infection that the potential risks of breastfeeding include: (1) HIV-1 transmission (in HIV‑1–negative infants), (2) developing viral resistance (in HIV‑1–positive infants), and (3) adverse reactions in a breastfed infant similar to those seen in adults [see Use in Specific Populations (8.2)].

Missed Dose

Instruct patients that if they miss a dose of DOVATO, to take it as soon as they remember. Advise patients not to double their next dose or take more than the prescribed dose [see Dosage and Administration (2)].

DOVATO, EPIVIR, TIVICAY, and TRIUMEQ are trademarks owned by or licensed to the ViiV Healthcare group of companies.

The other brand listed is a trademark owned by or licensed to its respective owner and is not owned by or licensed to the ViiV Healthcare group of companies. The maker of this brand is not affiliated with and does not endorse the ViiV Healthcare group of companies or its products.
Manufactured for:

ViiV Healthcare
Durham, NC 27701

©2025 ViiV Healthcare group of companies or its licensor.

DVT:15PI

PATIENT INFORMATION

DOVATO (doe VAH toe)

(dolutegravir and lamivudine)
tablets

What is the most important information I should know about DOVATO?

If you have both human immunodeficiency virus-1 (HIV-1) infection and Hepatitis B virus (HBV) infection, DOVATO can cause serious side effects, including:

- Resistant HBV. Your healthcare provider will test you for HBV infection before you start treatment with DOVATO. If you have HIV-1 and hepatitis B, the HBV can change (mutate) during your treatment with DOVATO and become harder to treat (resistant). It is not known if DOVATO is safe and effective in people who have HIV-1 and HBV infection.
- Worsening of HBV infection. If you have HBV infection and take DOVATO, your HBV may get worse (flare-up) if you stop taking DOVATO. A “flare-up” is when your HBV infection suddenly returns in a worse way than before.
  - Do not run out of DOVATO. Refill your prescription or talk to your healthcare provider before your DOVATO is all gone.
  - Do not stop DOVATO without first talking to your healthcare provider.
  - If you stop taking DOVATO, your healthcare provider will need to check your health often and do blood tests regularly for several months to check your liver function and monitor your HBV infection. It may be necessary to give you a medicine to treat hepatitis B. Tell your healthcare provider about any new or unusual symptoms you may have after you stop taking DOVATO.

For more information about side effects, see “What are the possible side effects of DOVATO?”

What is DOVATO?

DOVATO is a prescription medicine that is used without other HIV-1 medicines to treat HIV-1 infection in adults and adolescents 12 years of age and older who weigh at least 55 pounds (25 kg):

- who have not received HIV-1 medicines in the past, or
- to replace their current HIV-1 medicines when their healthcare provider determines that they meet certain requirements.

HIV-1 is the virus that causes Acquired Immune Deficiency Syndrome (AIDS).

It is not known if DOVATO is safe and effective in children less than 12 years of age or weighing less than 55 pounds (25 kg).

Do not take DOVATO if you:

- have ever had an allergic reaction to a medicine that contains dolutegravir or lamivudine. See the end of this Patient Information for a complete list of ingredients in DOVATO.
- take dofetilide. Taking DOVATO and dofetilide can cause side effects that may be serious or life-threatening.

Before you take DOVATO, tell your healthcare provider about all of your medical conditions, including if you:

- have or have had liver problems, including hepatitis B or C infection.
- have kidney problems.
- are pregnant or plan to become pregnant. Talk to your healthcare provider about the benefits and risks of treatment with DOVATO during pregnancy.
- Pregnancy Registry. There is a pregnancy registry for those who take DOVATO during pregnancy. The purpose of this registry is to collect information about the health of you and your baby. Talk with your healthcare provider about how you can take part in this registry.
- are breastfeeding or plan to breastfeed. DOVATO passes to your baby in your breast milk. Talk with your healthcare provider about the following risks to your baby from breastfeeding during treatment with DOVATO:
  - the HIV-1 virus may pass to your baby if your baby does not have HIV-1 infection.
  - the HIV-1 virus may become harder to treat if your baby has HIV-1 infection.
  - your baby may get side effects from DOVATO.

Tell your healthcare provider about all the medicines you take, including prescription and over-the-counter medicines, vitamins, and herbal supplements.

Some medicines interact with DOVATO. Keep a list of your medicines and show it to your healthcare provider and pharmacist when you get a new medicine.

- You can ask your healthcare provider or pharmacist for a list of medicines that interact with DOVATO.
- Do not start taking a new medicine without telling your healthcare provider. Your healthcare provider can tell you if it is safe to take DOVATO with other medicines.

How should I take DOVATO?

- Take DOVATO 1 time a day exactly as your healthcare provider tells you.
- Take DOVATO with or without food.
- Do not change your dose or stop taking DOVATO without talking with your healthcare provider.
- If you take antacids, laxatives, or other medicines that contain aluminum, magnesium, or buffered medicines, DOVATO should be taken at least 2 hours before or 6 hours after you take these medicines.
- If you need to take iron or calcium supplements, including multivitamins that contain iron or calcium, by mouth during treatment with DOVATO:
  - You may take these supplements at the same time that you take DOVATO with food.
  - If you do not take these supplements with DOVATO and food, take DOVATO at least 2 hours before or 6 hours after you take these supplements.
- Do not miss a dose of DOVATO. If you miss a dose of DOVATO, take it as soon as you remember. Do not take 2 doses at the same time or take more than your prescribed dose.
- Stay under the care of a healthcare provider during treatment with DOVATO.
- Do not run out of DOVATO. The virus in your blood may increase and the virus may become harder to treat. When your supply starts to run low, get more from your healthcare provider or pharmacy.
- If you take too much DOVATO, call your healthcare provider or go to the nearest hospital emergency room right away.

What are the possible side effects of DOVATO?

DOVATO can cause serious side effects, including:

- See “What is the most important information I should know about DOVATO?”
- Allergic reactions. Call your healthcare provider right away if you develop a rash with DOVATO. Stop taking DOVATO and get medical help right away if you develop a rash with any of the following signs or symptoms:

- fever
- generally ill feeling
- tiredness
- muscle or joint aches
- blisters or sores in mouth

- blisters or peeling of the skin
- redness or swelling of the eyes
- swelling of the mouth, face, lips, or tongue
- problems breathing

- Liver problems. People with a history of hepatitis B or C virus may have an increased risk of developing new or worsening changes in certain liver tests during treatment with DOVATO. Liver problems, including liver failure, have also happened in people without a history of liver disease or other risk factors. Your healthcare provider may do blood tests to check your liver.
Tell your healthcare provider right away if you get any of the following signs or symptoms of liver problems:

- your skin or the white part of your eyes turns yellow (jaundice)
- dark or “tea-colored” urine
- light-colored stools (bowel movements)

- nausea or vomiting
- loss of appetite
- pain, aching, or tenderness on the right side of your stomach area

- Too much lactic acid in your blood (lactic acidosis). Too much lactic acid is a serious medical emergency that can lead to death.
  Tell your healthcare provider right away if you get any of the following symptoms that could be signs of lactic acidosis:

- feel very weak or tired
- unusual (not normal) muscle pain
- trouble breathing
- stomach pain with nausea and vomiting

- feel cold, especially in your arms and legs
- feel dizzy or light-headed
- have a fast or irregular heartbeat

- Lactic acidosis can also lead to severe liver problems, which can lead to death. Your liver may become large (hepatomegaly) and you may develop fat in your liver (steatosis). Tell your healthcare provider right away if you get any of the signs or symptoms of liver problems which are listed above under “Liver problems”. You may be more likely to get lactic acidosis or severe liver problems if you are female or very overweight (obese).
- Changes in your immune system (Immune Reconstitution Syndrome) can happen when you start taking HIV-1 medicines. Your immune system may get stronger and begin to fight infections that have been hidden in your body for a long time. Tell your healthcare provider right away if you start having new symptoms after you start taking DOVATO.

The most common side effects of DOVATO include:

- headache
- nausea
- diarrhea

- trouble sleeping
- tiredness
- anxiety

These are not all the possible side effects of DOVATO.

Call your doctor for medical advice about side effects. You may report side effects to FDA at 1‑800‑FDA‑1088.

How should I store DOVATO?

- Store DOVATO below 86°F (30°C).
- DOVATO comes in a child-resistant package.

Keep DOVATO and all medicines out of the reach of children.

General information about the safe and effective use of DOVATO.

Medicines are sometimes prescribed for purposes other than those listed in a Patient Information leaflet. Do not use DOVATO for a condition for which it was not prescribed. Do not give DOVATO to other people, even if they have the same symptoms that you have. It may harm them. You can ask your healthcare provider or pharmacist for information about DOVATO that is written for health professionals.

What are the ingredients in DOVATO?

Active ingredients: dolutegravir and lamivudine.

Inactive ingredients: magnesium stearate, mannitol, microcrystalline cellulose, povidone K29/32, sodium starch glycolate, sodium stearyl fumarate.

The tablet film-coating contains: hypromellose, polyethylene glycol, titanium dioxide.

Manufactured for:

ViiV Healthcare

Durham, NC 27701

Trademarks are owned by or licensed to the ViiV Healthcare group of companies.

©2024 ViiV Healthcare group of companies or its licensor.

DVT:11PIL

For more information go to www.DOVATO.com or call 1-877-844-8872.

This Patient Information has been approved by the U.S. Food and Drug Administration.

Revised: 4/2024

PACKAGE LABEL

Principal Display Panel

NDC 49702-246-33

Dovato

(dolutegravir and lamivudine)

Tablets, for oral use

50 mg/300 mg

Rx Only

Note to pharmacist:

Do not cover ALERT box with pharmacy label.

ALERT: Find out about medicines that should NOT be taken with DOVATO.

See prescribing information for dosage information.

Contents:

- 4 blisters of 7 tablets and 1 blister of 2 tablets
- Prescribing Information
- Patient Information

30 tablets

Do not accept if membrane seal under cap is missing or broken.

Mfd for:

ViiV Healthcare

Durham, NC 27701

by: GlaxoSmithKline,

Durham, NC 27701

Trademarks owned or licensed by ViiV Healthcare group of companies.

©2023 ViiV Healthcare group of companies or its licensor.

Rev. 10/23

62000000089925